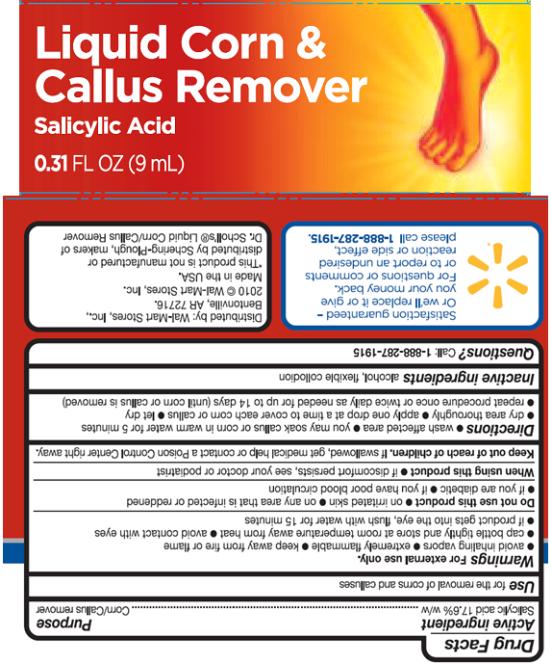 DRUG LABEL: Equate Corn and Callus Remover
NDC: 49035-151 | Form: LIQUID
Manufacturer: Wal-Mart Stores Inc.
Category: otc | Type: HUMAN OTC DRUG LABEL
Date: 20101004

ACTIVE INGREDIENTS: SALICYLIC ACID 170 mL/1 mL
INACTIVE INGREDIENTS: ALCOHOL; CAMPHOR (NATURAL); CASTOR OIL; ETHER; ETHYLCELLULOSE; MENTHOL; POLYSORBATE 80

Equate Corn and Callus Remover

Drug Facts

Active ingredient

Salicylic acid 17.6% w/w

Purpose

Corn/Callus remover

Use

for the removal of corn and calluses

Warnings

For external use only.

- avoid inhaling vapors
- extremely flammable
- keep away from fire or flame
- cap bottle tightly and store at room temperature away from heat
- avoid contact with eyes
- if product gets into the eye, flush with water for 15 minutes

Do not use

this product

- on irritated skin
- on any area that is infected or reddened
- if you are diabetic
- if you have poor blood circulation

When using this product

- if discomfort persists, see your doctor or podiatrist

Keep out of reach of children.

If swallowed, get medical help or contact a Poison Control Center right away.

Directions

- wash affected area
- you may soak callus or corn in warm water for 5 minutes
- dry area thoroughly
- apply one drop at a time to cover each corn or callus
- let dry
- repeat procedure once or twice daily as needed for up to 14 days (until corn or callus is removed)

Inactive ingredients

alcohol, flexible collodion

Questions?

call 1-888-287-1915

PRINCIPAL DISPLAY PANEL

Liquid Corn &
Callus Remover
Salicylic Acid
0.31 FL OZ (9 mL)